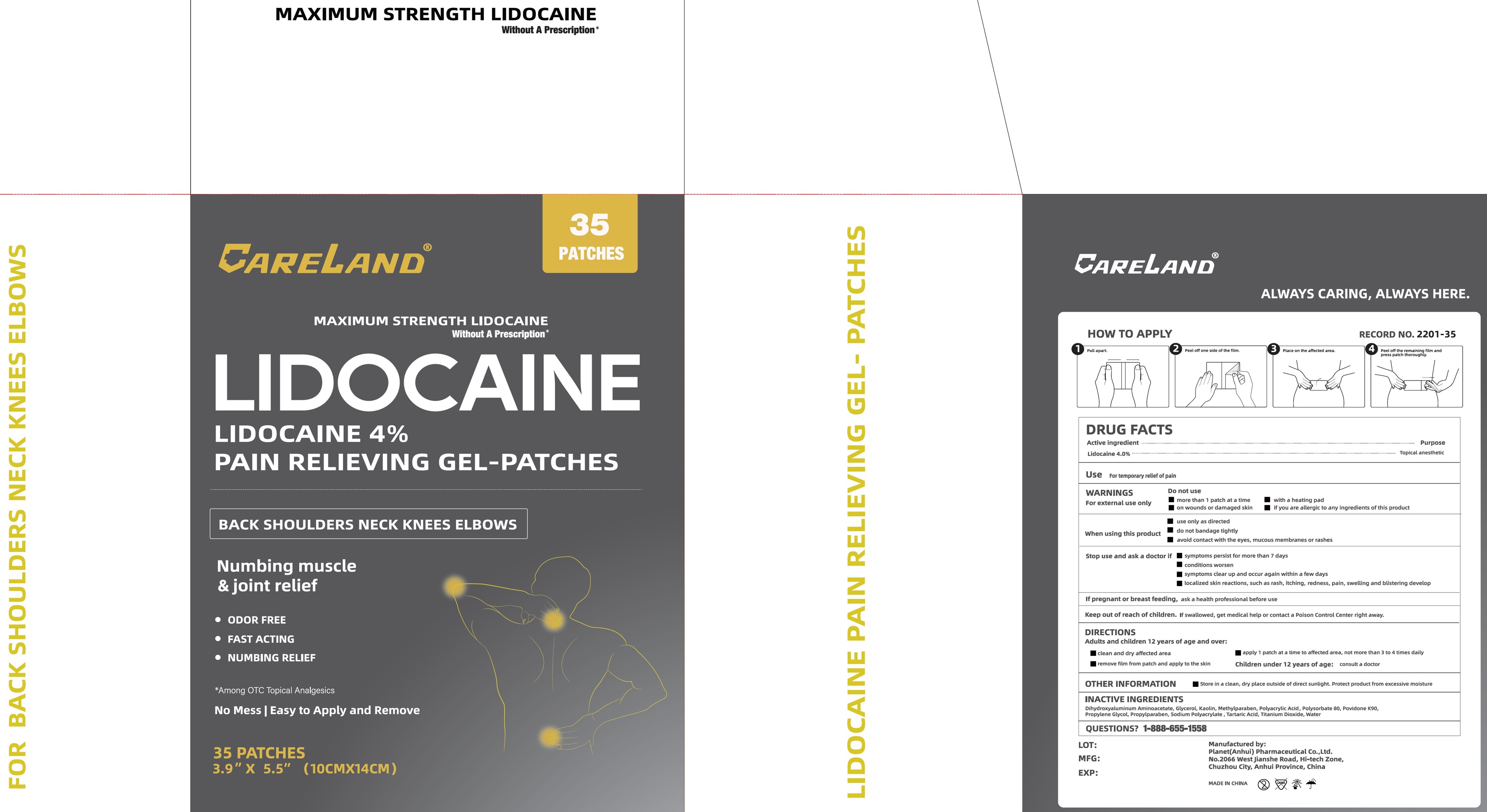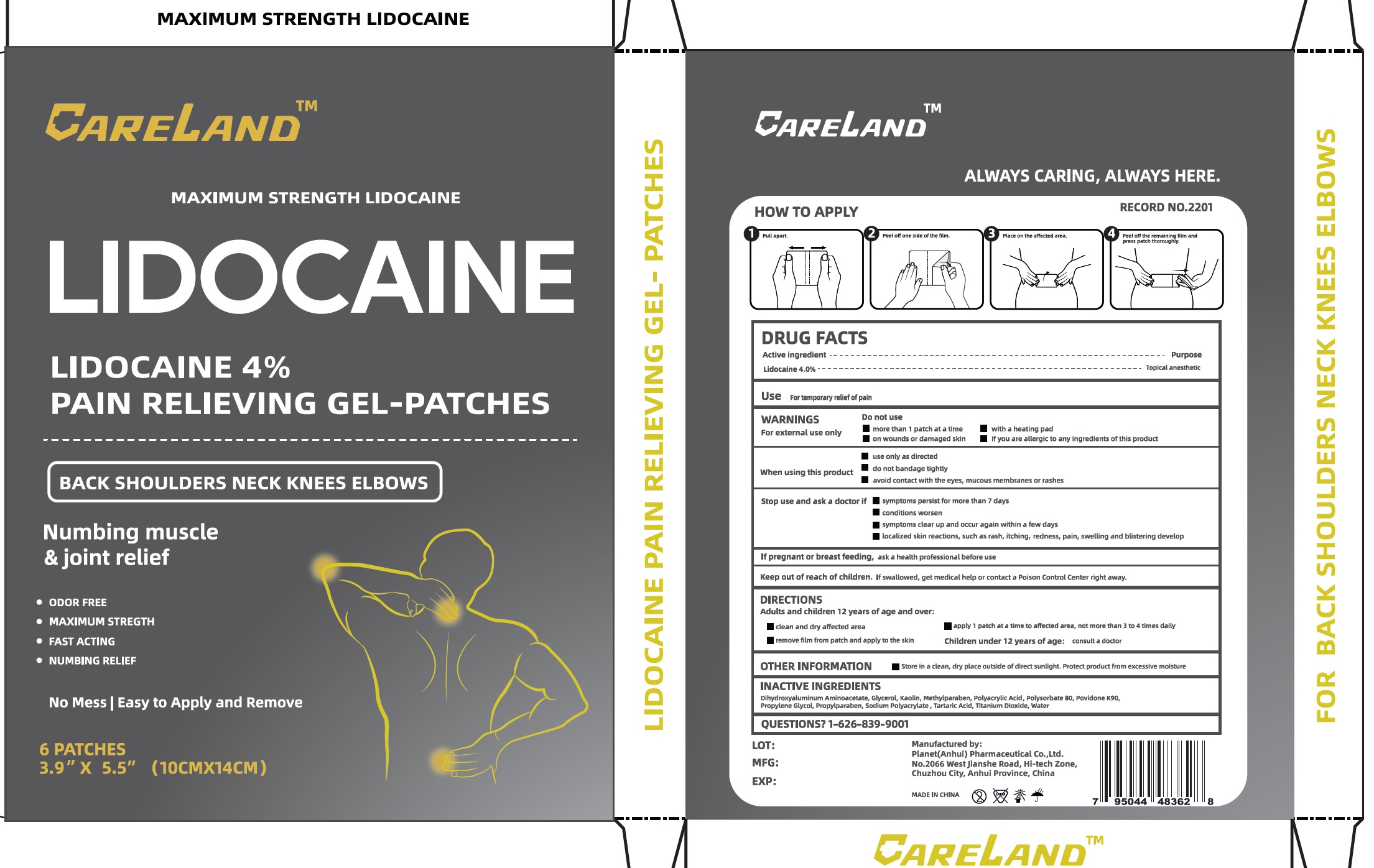 DRUG LABEL: Careland Lidocaine 4 Pain Relieving Gel-Patches
NDC: 75568-004 | Form: PATCH
Manufacturer: Planet (Anhui) Pharmaceutical Co., Ltd.
Category: otc | Type: HUMAN OTC DRUG LABEL
Date: 20260115

ACTIVE INGREDIENTS: LIDOCAINE 40 mg/1 g
INACTIVE INGREDIENTS: DIHYDROXYALUMINUM AMINOACETATE; GLYCERIN; KAOLIN; METHYLPARABEN; POLYSORBATE 80; POVIDONE K90; PROPYLENE GLYCOL; PROPYLPARABEN; TARTARIC ACID; TITANIUM DIOXIDE; WATER

Careland Lidocaine 4% Pain Relieving Gel-Patches

Active Ingredient

Lidocaine 4.0%

Purpose

Topical anesthetic

Use

For temporary relief of pain

WARNINGS

For external use only

Do not use

- more than 1 patch at a time
- with a heating pad
- on wounds or damaged skin
- ir you are allergic to any ingredients of this product

When using this product

- use only as directed
- do not bandage tightly
- avoid contact with the eyes, mucous membranes or rashes

Stop use and ask a doctor if

- symptoms persist for more than 7 days
- conditions worsen
- symptoms clear up and occur again within a few days
- localized skin reactions, such as rash, itching, redness, pain, swelling and blistering develop

If pregnant or breast feeding,

ask a health professional before use

Keep out of reach of children.

If swallowed, get medical help or contact a Poison Control Center right away.

DIRECTIONS

Adults and children 12 years of age and over:

- clean and dry affected area
- apply 1 patch at a time to affected area, not more than 3 to 4 times daily
- remove film from patch and apply to the skin
- Children under 12 years of age: consult a doctor

OTHER INFORMATION

- store in a clean, dry place outside of direct sunlight, Protect product from excessive moisture

INACTIVE INGREDIENTS

Dihydroxyaluminum Aminoacetate, Glycerol, Kaolin, Methylparaben, Polyacrylic Acid, Polysorbate 80, Povidone K90, Propylene Glycol, Propylparaben, Sodium Polyacrylate, Tartaric Acid, Titanium Dioxide, Water

QUESTIONS?

1-888-655-1558